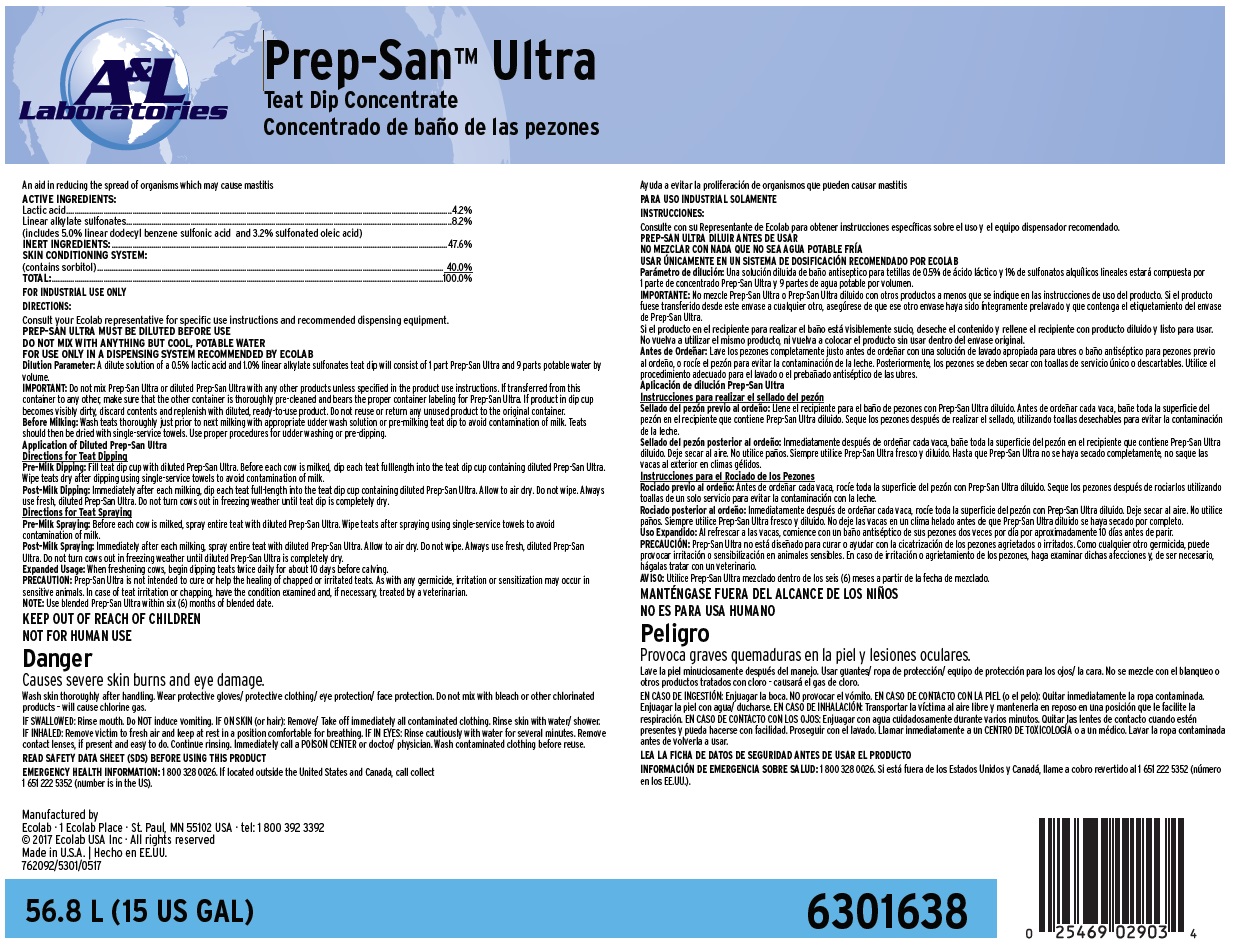 DRUG LABEL: Prep-San Ultra
NDC: 47593-547 | Form: SOLUTION
Manufacturer: Ecolab Inc.
Category: animal | Type: OTC ANIMAL DRUG LABEL
Date: 20251002

ACTIVE INGREDIENTS: LACTIC ACID 42 mg/1 mL; DODECYLBENZENESULFONIC ACID 50 mg/1 mL; SULFONATED OLEIC ACID 32 mg/1 mL
INACTIVE INGREDIENTS: WATER; SORBITOL

SAFE HANDLING WARNING

Danger

Causes severe skin burns and eye damage.

Wash skin thoroughly after handling. Wear protective gloves/ protective clothing/ eye protection/ face protection. Do not mix with bleach or other chlorinated products – will cause chlorine gas.

IF SWALLOWED: Rinse mouth. Do NOT induce vomiting. IF ON SKIN (or hair): Remove/ Take off immediately all contaminated clothing. Rinse skin with water/ shower.

IF INHALED: Remove victim to fresh air and keep at rest in a position comfortable for breathing. IF IN EYES: Rinse cautiously with water for several minutes. Remove

contact lenses, if present and easy to do. Continue rinsing. Immediately call a POISON CENTER or doctor/ physician. Wash contaminated clothing before reuse.

DIRECTIONS:

Consult your Ecolab representative for specific use instructions and recommended dispensing equipment.

PREP-SAN ULTRA MUST BE DILUTED BEFORE USE

DO NOT MIX WITH ANYTHING BUT COOL, POTABLE WATER

FOR USE ONLY IN A DISPENSING SYSTEM RECOMMENDED BY ECOLAB

Dilution Parameter: A dilute solution of a 0.5% lactic acid and 1.0% linear alkylate sulfonates teat dip will consist of 1 part Prep-San Ultra and 9 parts potable water by volume.

IMPORTANT: Do not mix Prep-San Ultra or diluted Prep-San Ultra with any other products unless specified in the product use instructions. If transferred from this container to any other, make sure that the other container is thoroughly pre-cleaned and bears the proper container labeling for Prep-San Ultra. If product in dip cup becomes visibly dirty, discard contents and replenish with diluted, ready-to-use product. Do not reuse or return any unused product to the original container.

Before Milking: Wash teats thoroughly just prior to next milking with appropriate udder wash solution or pre-milking teat dip to avoid contamination of milk. Teats should then be dried with single-service towels. Use proper procedures for udder washing or pre-dipping.

Application of Diluted Prep-San Ultra

Directions for Teat Dipping

Pre-Milk Dipping: Fill teat dip cup with diluted Prep-San Ultra. Before each cow is milked, dip each teat fulllength into the teat dip cup containing diluted Prep-San Ultra. Wipe teats dry after dipping using single-service towels to avoid contamination of milk.

Post-Milk Dipping: Immediately after each milking, dip each teat full-length into the teat dip cup containing diluted Prep-San Ultra. Allow to air dry. Do not wipe. Always use fresh, diluted Prep-San Ultra. Do not turn cows out in freezing weather until teat dip is completely dry.

Directions for Teat Spraying

Pre-Milk Spraying: Before each cow is milked, spray entire teat with diluted Prep-San Ultra. Wipe teats after spraying using single-service towels to avoid contamination of milk.

Post-Milk Spraying: Immediately after each milking, spray entire teat with diluted Prep-San Ultra. Allow to air dry. Do not wipe. Always use fresh, diluted Prep-San Ultra. Do not turn cows out in freezing weather until diluted Prep-San Ultra is completely dry.

Expanded Usage: When freshening cows, begin dipping teats twice daily for about 10 days before calving.

PRECAUTION: Prep-San Ultra is not intended to cure or help the healing of chapped or irritated teats. As with any germicide, irritation or sensitization may occur in sensitive animals. In case of teat irritation or chapping, have the condition examined and, if necessary, treated by a veterinarian.

NOTE: Use blended Prep-San Ultra within six (6) months of blended date.

OTHER SAFETY INFORMATION

READ SAFETY DATA SHEET (SDS) BEFORE USING THIS PRODUCT

EMERGENCY HEALTH INFORMATION: 1 800 328 0026. If located outside the United States and Canada, call collect
1 651 222 5352 (number is in the US).

PACKAGE LABEL

A & L Laboratories

Prep-San™ Ultra

Teat Dip Concentrate

An aid in reducing the spread of organisms which may cause mastitis

ACTIVE INGREDIENTS:

Lactic acid................................................................................................4.2%

Linear alkylate sulfonates........................................................................8.2%

(includes 5.0% linear dodecyl benzene sulfonic acid and 3.2% sulfonated oleic acid)

INERT INGREDIENTS:................................................................................47.6%

SKIN CONDITIONING SYSTEM:

(contains sorbitol).................................................................................... 40.0%

TOTAL:.....................................................................................................100.0%

Manufactured by

Ecolab · 1 Ecolab Place · St. Paul, MN 55102 USA · tel: 1 800 392 3392

© 2017 Ecolab USA Inc · All rights reserved

Made in U.S.A. | Hecho en EE.UU.

762092/5301/0517

56.8 L (15 US GAL) 6301638